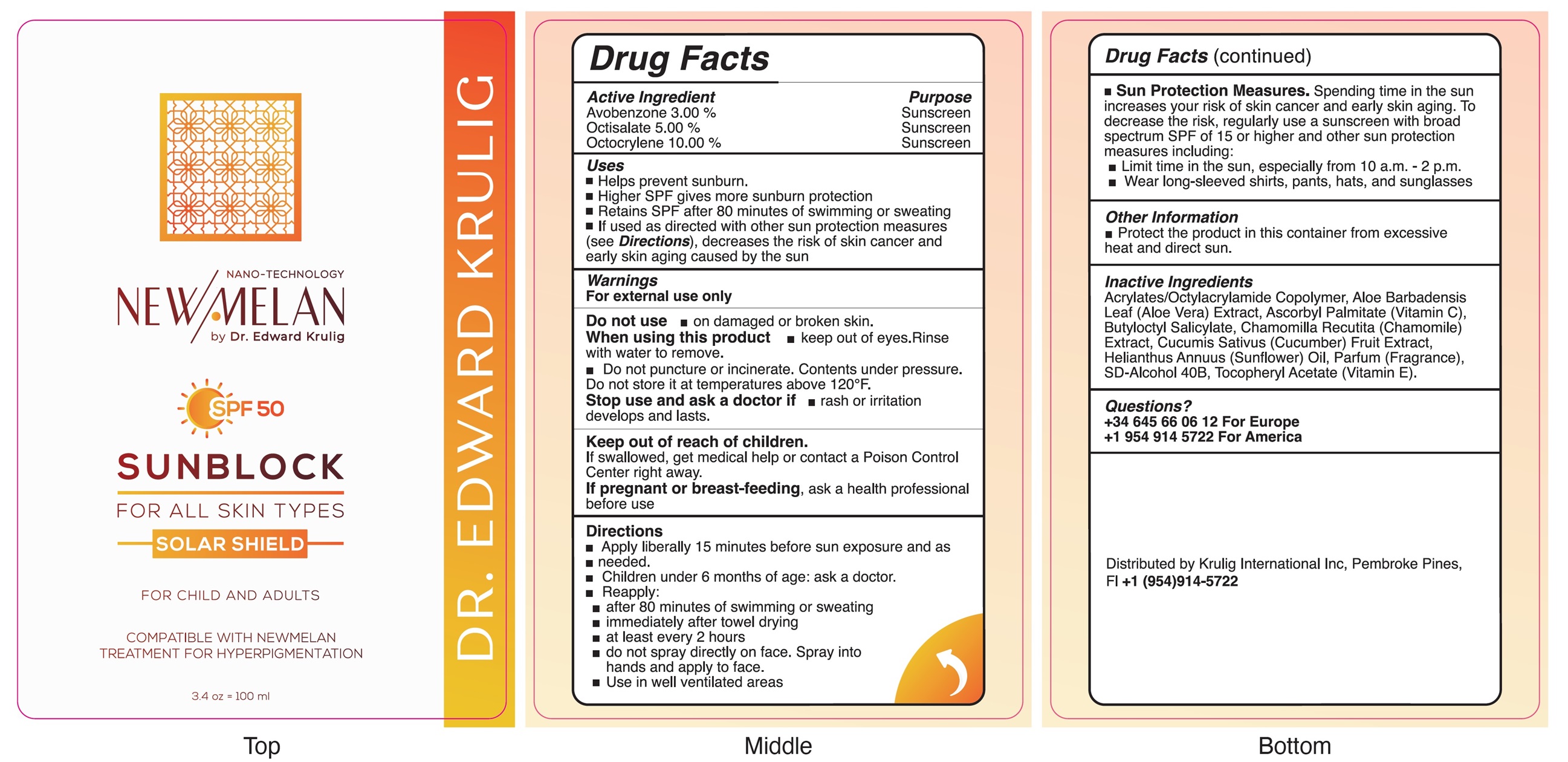 DRUG LABEL: Dr Edward Krulig New Melan Sunblock SPF 50
NDC: 84857-545 | Form: LIQUID
Manufacturer: KRULIG INTERNATIONAL, INC
Category: otc | Type: HUMAN OTC DRUG LABEL
Date: 20241031

ACTIVE INGREDIENTS: AVOBENZONE 30 mg/1 mL; OCTISALATE 50 mg/1 mL; OCTOCRYLENE 100 mg/1 mL
INACTIVE INGREDIENTS: ALOE VERA LEAF; ASCORBYL PALMITATE; BUTYLOCTYL SALICYLATE; CHAMOMILE; CUCUMBER; HELIANTHUS ANNUUS FLOWERING TOP; .ALPHA.-TOCOPHEROL ACETATE

Dr. Edward Krulig New Melan Sunblock SPF 50

Active Ingredient

Avobenzone 3.00%

Octisalate 5.00%

Octocrylene 10.00%

Purpose

Sunscreen

Uses

- Helps prevent sunburn.
- Higher SPF gives more sunburn protection
- Retains SPF after 80 minutes of swimming or sweating
- If used as directed with other sun protection measures (see Directions), decreases the risk of skin cancer and early skin aging caused by the sun

Warnings

For external use only

Do not use

- on damaged or broken skin.

When using this product

- keep out of eyes.Rinse with water to remove.
- Do not puncture or incinerate. Contents under pressure.

Do not store it at temperatures above 120°F.

Stop use and ask a doctor if

- rash or irritation develops and lasts.

Keep out of reach of children.

If swallowed, get medical help or contact a Poison Control Center right away.

If pregnant or breast-feeding,

ask a health professional before use

Directions

- Apply liberally 15 minutes before sun exposure and as
- needed.
- Children under 6 months of age: ask a doctor.
- Reapply:
- after 80 minutes of swimming or sweating
- immediately after towel drying
- at least every 2 hours
- do not spray directly on face. Spray into hands and apply to face.
- Use in well-ventilated areas
- Sun Protection Measures. Spending time in the sun increases your risk of skin cancer and early skin aging. To decrease the risk, regularly use a sunscreen with broad spectrum SPF of 15 or higher and other sun protection measures including:
- Limit time in the sun, especially from 10 a.m. - 2 p.m.
- Wear long-sleeved shirts, pants, hats, and sunglasses

Other Information

- Protect the product in this container from excessive heat and direct sun.

Inactive Ingredients

Acrylates/Octylacrylamide Copolymer, Aloe Barbadensis Leaf (Aloe Vera) Extract, Ascorbyl Palmitate (Vitamin C), Butyloctyl Salicylate, Chamomilla Recutita (Chamomile) Extract, Cucumis Sativus (Cucumber) Fruit Extract, Helianthus Annuus (Sunflower) Oil, Parfum (Fragrance), SD-Alcohol 40B, Tocopheryl Acetate (Vitamin E).

Questions?

+34 645 66 06 12 For Europe
+1 954 914 5722 For America